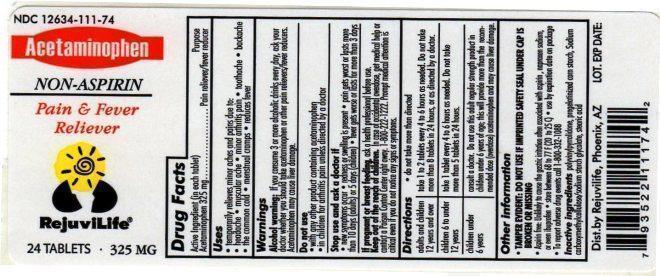 DRUG LABEL: Acetaminophen
NDC: 12634-111 | Form: TABLET
Manufacturer: Apotheca, Inc
Category: otc | Type: HUMAN OTC DRUG LABEL
Date: 20130729

ACTIVE INGREDIENTS: ACETAMINOPHEN 325 mg/1 1
INACTIVE INGREDIENTS: POVIDONES; STARCH, CORN; STARCH, POTATO; STEARIC ACID

ACETAMINOPHEN TABLET 325MG

DRUG FACTS: ACTIVE INGREDIENT

Acetaminophen 325mg

USES

Temporarily relieves minor aches and pains due to

- the common cold
- headache
- backache
- minor pain of arthritis
- toothache
- muscular aches
- menstrual cramps

Temporarily reduces fever

INDICATIONS & USAGE

do not take more then directed

adults and children 12 years and over

take 1 to 2 tablets every 4 to 6 hours as needed. Do not take more than 8 tablets in 24 hours.

children 6 to under 12 years

take 1 tablet every 4 to 6 hours as needed. Do not take nore than 5 tablets in 24 hours

children under 6 years

consult a doctor. Do not use this adult regular strength product in children under 6 years of age, this will provide more than the recommended dose (overdose) acetominophen and may cause liver damage.

Tamper Evident: do not use if imprinted safety seal under cap is broken or missingStore between 20-25oC (68-77oF)Use by expiration date on packageTo report adverse drug events call 1-800-332-1088

WARNINGS

Liver warning:This product contains acetaminophen. Severe liver damage may occur if

- Adult takes more than 12 tablets in 24 hours, which is the maximum daily amount
- Child takes more than 5 doses in 24 hours
- Taken with other drugs containing acetaminophen
- Adult has 3 or more alcoholic drinks every day while using this product

Do not use

- With any other drug containing acetaminophen (prescription or nonprescription). If you are not sure whether a drug contains acetaminophen, ask a doctor or pharmacist
- if you are allergic to acetaminophen or any of the inactive ingredients in this product

Ask a doctor before use if you have

liver disease.

Ask a doctor or pharmacist before use if you are

taking the blood thinning drug warfarin.

Stop use and ask a doctor if

- Pain gets worse or lasts more than 10 days in adults and children
- Pain gets worse or lasts more than 5 days in children under 12 years
- Fever gets worse or lasts more than 3 days
- New symptoms occur
- Redness or swelling is present

These could be sign of a serious condition.

If pregnant or breast-feeding,

ask a health professional before use.

Overdose warning:

Taking more than the recommended dose (overdose) may cause liver damage. In the case of accidental overdose, get medical help or contact a Poison Control Center right away.

DOSAGE & ADMINISTRATION

Directions

- do not take more than directed (see overdose warning).

Adults and children 12 years and over | Take 2 tablets every 4 to 6 while symptoms last. Do not take more than 12 tablets in 24 hours.
Children 6 to under 12 years | Take 1 tablet every 4 to 6 while symptoms last. Do not take more than 5 tablets in 24 hours.
Children under 6 years | Do not use adult regular strength products in childern under 6 years of age; this will provide more than the recommended dose (overdose) and may cause liver damage.

Other information

- Tamper Evident: do not use if imprinted safety seal under cap is broken or missing
- store between 20-25°C (68-77°F)
- use by expiration date on package

INACTIVE INGREDIENTS

Povidone, pregelatinized starch, sodium starch glycolate, stearic acid

PRINCIPAL DISPLAY PANEL

NDC 12634-111-74

Acetaminophen

NON-ASPIRIN

Pain & Fever

Reliever

RejuviLife

24 TABLETS 325 MG

Distributed by:

RejuviLife, Phoenix, AZ

RejuviLife is a trademark of Apotheca, Inc